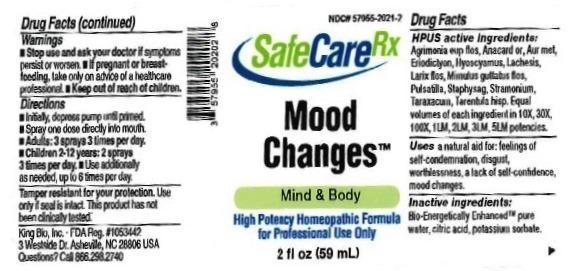 DRUG LABEL: Mood Changes
NDC: 57955-2021 | Form: LIQUID
Manufacturer: King Bio Inc.
Category: homeopathic | Type: HUMAN OTC DRUG LABEL
Date: 20161213

ACTIVE INGREDIENTS: AGRIMONIA EUPATORIA FLOWER 10 [hp_X]/59 mL; SEMECARPUS ANACARDIUM JUICE 10 [hp_X]/59 mL; GOLD 10 [hp_X]/59 mL; ERIODICTYON CALIFORNICUM LEAF 10 [hp_X]/59 mL; HYOSCYAMUS NIGER 10 [hp_X]/59 mL; LACHESIS MUTA VENOM 10 [hp_X]/59 mL; LARIX DECIDUA FLOWERING TOP 10 [hp_X]/59 mL; MIMULUS GUTTATUS FLOWERING TOP 10 [hp_X]/59 mL; PULSATILLA VULGARIS 10 [hp_X]/59 mL; DELPHINIUM STAPHISAGRIA SEED 10 [hp_X]/59 mL; DATURA STRAMONIUM 10 [hp_X]/59 mL; TARAXACUM OFFICINALE 10 [hp_X]/59 mL; LYCOSA TARANTULA 10 [hp_X]/59 mL
INACTIVE INGREDIENTS: WATER; CITRIC ACID MONOHYDRATE; POTASSIUM SORBATE

Mood Changes™

ACTIVE INGREDIENT

Drug Facts__________________________________________________________________________________________________________

HPUS active ingredients: Agrimonia eupatoria, flos, Anacardium orientale, Aurum metallicum, Eriodictyon californicum, Hyoscyamus niger, Lachesis mutus, Larix decidua, flos, Mimulus guttatus, flos, Pulsatilla, Staphysagria, Stramonium, Taraxacum officinale, Tarentula hispana. Equal volumes of each ingredient in 10X, 30X, 100X, 1LM, 2LM, 3LM, 5LM potencies.

INDICATIONS AND USAGE

Uses a natural aid for: feeling of self-condemnation, disgust, worthlessness, a lack of self-confidence, mood changes.

INACTIVE INGREDIENT

Inactive Ingredients: Bio-Energetically Enhanced™ pure water, citric acid and potassium sorbate.

Warnings

- Stop use and ask your doctor if symptoms persist or worsen.
- If pregnant or breast-feeding, take only on advice of a healthcare professional.

- Keep out of reach of children.

Directions

- Initially, depress pump until primed.
- Spray one dose directly into mouth.
- Adults: 3 sprays 3 times per day.
- Children 2-12: 2 sprays 3 times per day.
- Use additionally as needed, up to 6 times per day.

OTHER SAFETY INFORMATION

Tamper resistant for your protection. Use only if seal is intact. This product has not been clinically tested.

PURPOSE

Uses a natural aid for:

- feeling of self-condemnation
- disgust
- worthlessness
- a lack of self-confidence
- mood changes